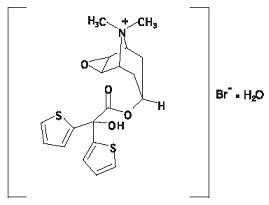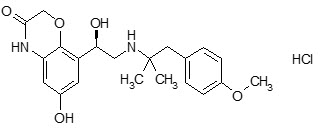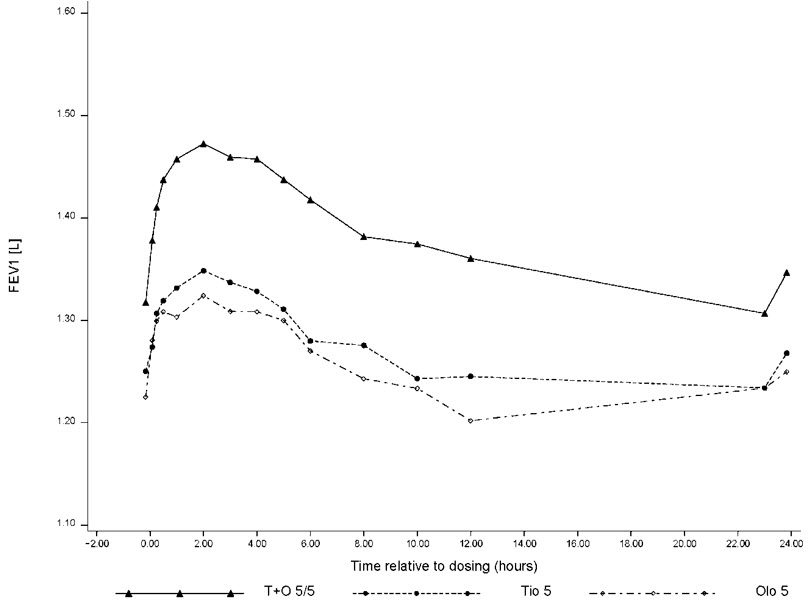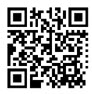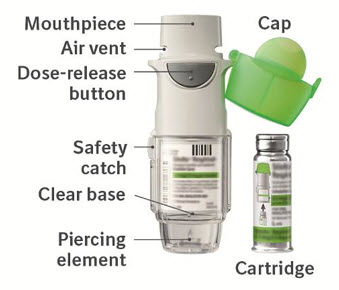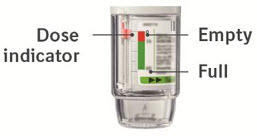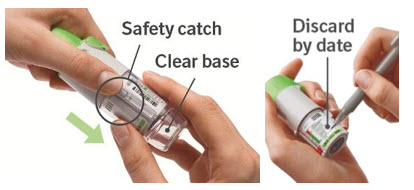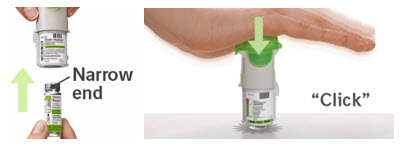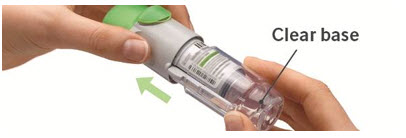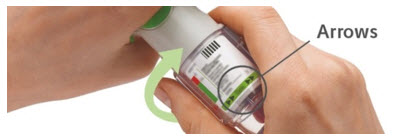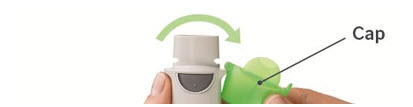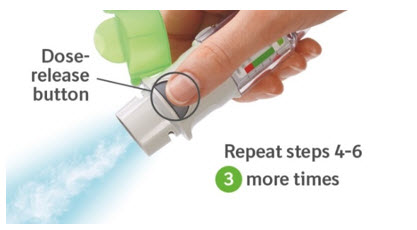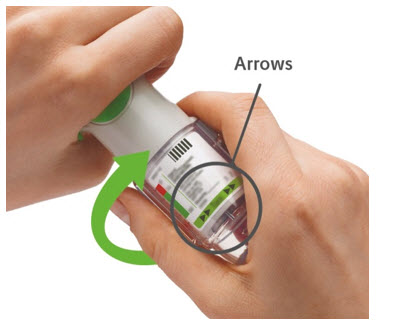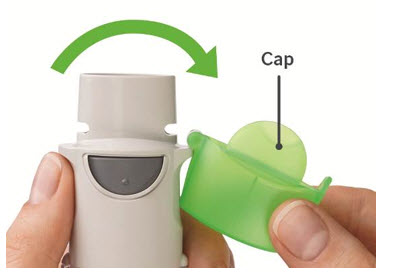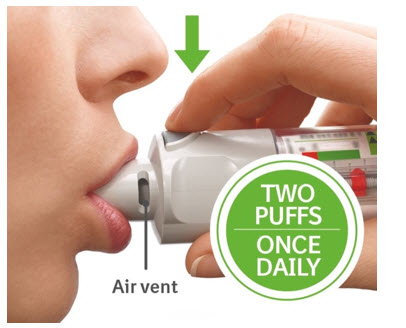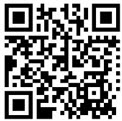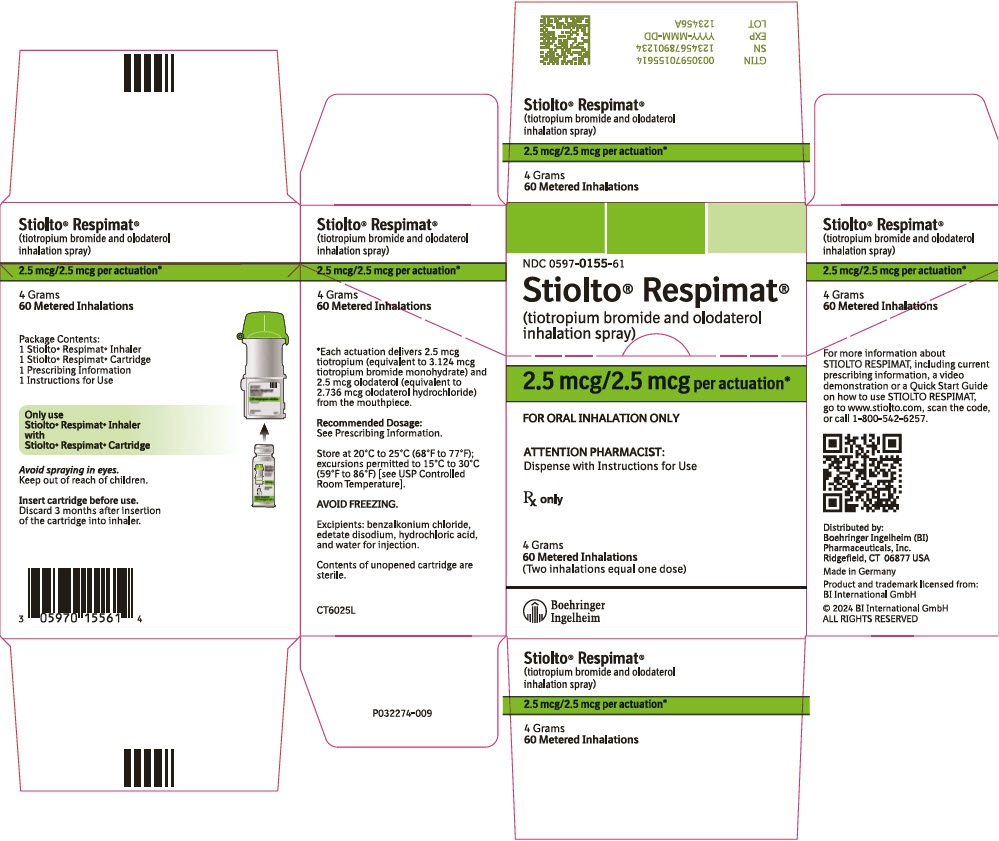 DRUG LABEL: Stiolto Respimat
NDC: 0597-0155 | Form: SPRAY, METERED
Manufacturer: Boehringer Ingelheim Pharmaceuticals, Inc.
Category: prescription | Type: HUMAN PRESCRIPTION DRUG LABEL
Date: 20250630

ACTIVE INGREDIENTS: TIOTROPIUM BROMIDE MONOHYDRATE 3.124 ug/1 1; OLODATEROL HYDROCHLORIDE 2.736 ug/1 1

HIGHLIGHTS OF PRESCRIBING INFORMATION

These highlights do not include all the information needed to use STIOLTO RESPIMAT safely and effectively. See full prescribing information for STIOLTO RESPIMAT.
STIOLTO® RESPIMAT® (tiotropium bromide and olodaterol inhalation spray), for oral inhalation use
Initial U.S. Approval: 2015

1 INDICATIONS AND USAGE

STIOLTO RESPIMAT is a combination of tiotropium bromide, an anticholinergic and olodaterol, a long-acting beta2-adrenergic agonist (LABA) indicated for the long-term, once-daily maintenance treatment of patients with chronic obstructive pulmonary disease (COPD). (1.1)

Important limitations:

- STIOLTO RESPIMAT is NOT indicated to treat acute deterioration of COPD. (1.1)
- STIOLTO RESPIMAT is NOT indicated to treat asthma. (1.1)

2 DOSAGE AND ADMINISTRATION

- For oral inhalation only.
- Two inhalations of STIOLTO RESPIMAT once-daily at the same time of day. (2)

3 DOSAGE FORMS AND STRENGTHS

Inhalation spray: Each actuation from the mouthpiece delivers 2.5 mcg tiotropium (equivalent to 3.124 mcg tiotropium bromide monohydrate), and 2.5 mcg olodaterol (equivalent to 2.736 mcg olodaterol hydrochloride). Two actuations equal one dose. (3)

4 CONTRAINDICATIONS

- Use of a LABA, including STIOLTO RESPIMAT, without an inhaled corticosteroid is contraindicated in patients with asthma. (4)
- Hypersensitivity to tiotropium, ipratropium, olodaterol, or any component of this product. (4)

5 WARNINGS AND PRECAUTIONS

- LABA as monotherapy (without an inhaled corticosteroid) for asthma increases the risk of serious asthma-related events. (5.1)
- Do not initiate STIOLTO RESPIMAT in acutely deteriorating COPD patients. (5.2)
- Do not use for relief of acute symptoms. Concomitant short-acting beta2-agonists can be used as needed for acute relief. (5.2)
- Do not exceed the recommended dosage. Excessive use of STIOLTO RESPIMAT, or use in conjunction with other medications containing LABA can result in clinically significant cardiovascular effects and may be fatal. (5.3)
- Immediate hypersensitivity reactions: Discontinue STIOLTO RESPIMAT at once and consider alternatives if immediate hypersensitivity reactions, including angioedema, urticaria, rash, bronchospasm, or anaphylaxis, occur. (5.4)
- Life-threatening paradoxical bronchospasm can occur. Discontinue STIOLTO RESPIMAT immediately. (5.5)
- Use with caution in patients with cardiovascular or convulsive disorders, thyrotoxicosis, or sensitivity to sympathomimetic drugs. (5.6, 5.7)
- Worsening of narrow-angle glaucoma may occur. Use with caution in patients with narrow-angle glaucoma and instruct patients to consult a physician immediately if this occurs. (5.8)
- Worsening of urinary retention may occur. Use with caution in patients with prostatic hyperplasia or bladder-neck obstruction and instruct patients to consult a physician immediately if this occurs. (5.9)
- Be alert to hypokalemia and hyperglycemia. (5.11)

6 ADVERSE REACTIONS

The most common adverse reactions (>3% incidence and more than an active control) were nasopharyngitis, cough, and back pain. (6)

To report SUSPECTED ADVERSE REACTIONS, contact Boehringer Ingelheim Pharmaceuticals, Inc. at 1-800-542-6257 or FDA at 1-800-FDA-1088 or www.fda.gov/medwatch.

7 DRUG INTERACTIONS

- Other adrenergic drugs may potentiate effect. Use with caution. (5.3, 7.1)
- Xanthine derivatives, steroids, diuretics, or non-potassium sparing diuretics may potentiate hypokalemia or ECG changes. Use with caution. (7.2, 7.3)
- MAO inhibitors, tricyclic antidepressants, and drugs that prolong QTc interval may potentiate effect on cardiovascular system. Use with extreme caution. (7.4)
- Beta-blockers may decrease effectiveness. Use with caution and only when medically necessary. (7.5)
- Anticholinergics: May interact additively with concomitantly used anticholinergic medications. Avoid administration of STIOLTO RESPIMAT with other anticholinergic-containing drugs. (7.6)

8 USE IN SPECIFIC POPULATIONS

Patients with moderate to severe renal impairment should be monitored closely for potential anticholinergic side effects. (2, 8.7)

FULL PRESCRIBING INFORMATION

1 INDICATIONS AND USAGE

1.1 Maintenance Treatment of COPD

STIOLTO RESPIMAT is a combination of tiotropium bromide and olodaterol indicated for long-term, once-daily maintenance treatment of patients with chronic obstructive pulmonary disease (COPD), including chronic bronchitis and/or emphysema.

Important Limitations of Use

- STIOLTO RESPIMAT is not indicated to treat acute deteriorations of COPD [see Warnings and Precautions (5.2)].
- STIOLTO RESPIMAT is not indicated to treat asthma. The safety and effectiveness of STIOLTO RESPIMAT in asthma have not been established.

2 DOSAGE AND ADMINISTRATION

2.1 Recommended Dosage

The recommended dosage of STIOLTO RESPIMAT is two inhalations once-daily at the same time of the day. Do not use STIOLTO RESPIMAT more than two inhalations every 24 hours.

2.2 Administration Information

For oral inhalation only.

Prior to first use, the STIOLTO RESPIMAT cartridge is inserted into the STIOLTO RESPIMAT inhaler and the unit is primed. When using the unit for the first time, patients are to actuate the inhaler toward the ground until an aerosol cloud is visible and then repeat the process three more times. The unit is then considered primed and ready for use. If not used for more than 3 days, patients are to actuate the inhaler once to prepare the inhaler for use. If not used for more than 21 days, patients are to actuate the inhaler until an aerosol cloud is visible and then repeat the process three more times to prepare the inhaler for use [see Patient Counseling Information (17)].

No dosage adjustment is required for geriatric, hepatically-impaired, or renally-impaired patients. However, patients with moderate to severe renal impairment given STIOLTO RESPIMAT should be monitored closely for anticholinergic effects [see Warnings and Precautions (5.10), Use in Specific Populations (8.5, 8.6, 8.7), and Clinical Pharmacology (12.3)].

3 DOSAGE FORMS AND STRENGTHS

Inhalation Spray: STIOLTO RESPIMAT consists of a STIOLTO RESPIMAT inhaler and an aluminum cylinder (STIOLTO RESPIMAT cartridge) containing a combination of tiotropium bromide (as the monohydrate) and olodaterol (as the hydrochloride). The STIOLTO RESPIMAT cartridge is intended only for use with the STIOLTO RESPIMAT inhaler.

Each actuation from the STIOLTO RESPIMAT inhaler delivers 2.5 mcg tiotropium (equivalent to 3.124 mcg tiotropium bromide monohydrate) and 2.5 mcg olodaterol (equivalent to 2.736 mcg olodaterol hydrochloride) from the mouthpiece.

Two actuations equal one dose.

4 CONTRAINDICATIONS

Use of a LABA, including STIOLTO RESPIMAT, without an inhaled corticosteroid is contraindicated in patients with asthma [see Warnings and Precautions (5.1)]. STIOLTO RESPIMAT is not indicated for the treatment of asthma.

STIOLTO RESPIMAT is contraindicated in patients with a hypersensitivity to tiotropium, ipratropium, olodaterol, or any component of this product [see Warnings and Precautions (5.4)].

In clinical trials and postmarketing experience with tiotropium, immediate hypersensitivity reactions, including angioedema (including swelling of the lips, tongue, or throat), itching, or rash have been reported. Hypersensitivity reactions were also reported in clinical trials with STIOLTO RESPIMAT.

5 WARNINGS AND PRECAUTIONS

5.1 Serious Asthma-Related Events – Hospitalizations, Intubations, Death

- The safety and efficacy of STIOLTO RESPIMAT in patients with asthma have not been established. STIOLTO RESPIMAT is not indicated for the treatment of asthma [see Contraindications (4)].
- Use of long-acting beta2-adrenergic agonists (LABA) as monotherapy [without inhaled corticosteroids (ICS)] for asthma is associated with an increased risk of asthma-related death. Available data from controlled clinical trials also suggest that use of LABA as monotherapy increases the risk of asthma-related hospitalization in pediatric and adolescent patients. These findings are considered a class effect of LABA monotherapy. When LABA are used in fixed-dose combination with ICS, data from large clinical trials do not show a significant increase in the risk of serious asthma-related events (hospitalizations, intubations, death) compared with ICS alone.
- A 28-week, placebo-controlled US study comparing the safety of another LABA (salmeterol) with placebo, each added to usual asthma therapy, showed an increase in asthma-related deaths in patients receiving salmeterol (13/13,176 in patients treated with salmeterol vs. 3/13,179 in patients treated with placebo; RR 4.37, 95% CI 1.25, 15.34). The increased risk of asthma-related death is considered a class effect of LABA, including olodaterol, one of the active ingredients in STIOLTO RESPIMAT.
- No study adequate to determine whether the rate of asthma-related death is increased in patients treated with STIOLTO RESPIMAT has been conducted.
- Available data do not suggest an increased risk of death with use of LABA in patients with COPD.

5.2 Deterioration of Disease and Acute Episodes

STIOLTO RESPIMAT should not be initiated in patients with acutely deteriorating COPD, which may be a life-threatening condition. STIOLTO RESPIMAT has not been studied in patients with acutely deteriorating COPD. The use of STIOLTO RESPIMAT in this setting is inappropriate.

STIOLTO RESPIMAT should not be used for the relief of acute symptoms, i.e., as rescue therapy for the treatment of acute episodes of bronchospasm. STIOLTO RESPIMAT has not been studied in the relief of acute symptoms and extra doses should not be used for that purpose. Acute symptoms should be treated with an inhaled short-acting beta2-agonist.

When beginning STIOLTO RESPIMAT, patients who have been taking inhaled, short-acting beta2-agonists on a regular basis (e.g., four times a day) should be instructed to discontinue the regular use of these drugs and use them only for symptomatic relief of acute respiratory symptoms. When prescribing STIOLTO RESPIMAT, the healthcare provider should also prescribe an inhaled, short-acting beta2-agonist and instruct the patient on how it should be used. Increasing inhaled beta2-agonist use is a signal of deteriorating disease for which prompt medical attention is indicated.

COPD may deteriorate acutely over a period of hours or chronically over several days or longer. If STIOLTO RESPIMAT no longer controls symptoms of bronchoconstriction, or the patient's inhaled, short-acting beta2-agonist becomes less effective or the patient needs more inhalation of short-acting beta2-agonist than usual, these may be markers of deterioration of disease. In this setting, a re-evaluation of the patient and the COPD treatment regimen should be undertaken at once. Increasing the daily dosage of STIOLTO RESPIMAT beyond the recommended dosage is not appropriate in this situation.

5.3 Excessive Use of STIOLTO RESPIMAT and Use With Other Long-Acting Beta2-Agonists

As with other inhaled drugs containing beta2-adrenergic agents, STIOLTO RESPIMAT should not be used more often than recommended, at higher doses than recommended, or in conjunction with other medications containing long-acting beta2-agonists, as an overdose may result. Clinically significant cardiovascular effects and fatalities have been reported in association with excessive use of inhaled sympathomimetic drugs.

5.4 Immediate Hypersensitivity Reactions

Immediate hypersensitivity reactions, including urticaria, angioedema (including swelling of the lips, tongue or throat), rash, bronchospasm, anaphylaxis, or itching may occur after administration of STIOLTO RESPIMAT. If such a reaction occurs, therapy with STIOLTO RESPIMAT should be stopped at once and alternative treatments should be considered. Given the similar structural formula of atropine to tiotropium, patients with a history of hypersensitivity reactions to atropine or its derivatives should be closely monitored for similar hypersensitivity reactions to STIOLTO RESPIMAT.

5.5 Paradoxical Bronchospasm

As with other inhaled medicines, STIOLTO RESPIMAT may cause paradoxical bronchospasm that may be life-threatening. If paradoxical bronchospasm occurs, STIOLTO RESPIMAT should be stopped immediately and alternative therapy instituted.

5.6 Cardiovascular Effects

Olodaterol, like other beta2-agonists, can produce a clinically significant cardiovascular effect in some patients as measured by increases in pulse rate, systolic or diastolic blood pressure, and/or symptoms. If such effects occur, STIOLTO RESPIMAT may need to be discontinued. In addition, beta-agonists have been reported to produce ECG changes, such as flattening of the T wave, prolongation of the QTc interval, and ST segment depression. The clinical significance of these findings is unknown. Long acting beta2-adrenergic agonists should be administered with caution in patients with cardiovascular disorders, especially coronary insufficiency, cardiac arrhythmias, hypertrophic obstructive cardiomyopathy, and hypertension.

5.7 Coexisting Conditions

Olodaterol, like other sympathomimetic amines, should be used with caution in patients with convulsive disorders or thyrotoxicosis, in patients with known or suspected prolongation of the QT interval, and in patients who are unusually responsive to sympathomimetic amines. Doses of the related beta2-agonist albuterol, when administered intravenously, have been reported to aggravate pre-existing diabetes mellitus and ketoacidosis.

5.8 Worsening of Narrow-Angle Glaucoma

STIOLTO RESPIMAT should be used with caution in patients with narrow-angle glaucoma. Prescribers and patients should be alert for signs and symptoms of acute narrow-angle glaucoma (e.g., eye pain or discomfort, blurred vision, visual halos or colored images in association with red eyes from conjunctival congestion and corneal edema). Instruct patients to consult a physician immediately should any of these signs or symptoms develop.

5.9 Worsening of Urinary Retention

STIOLTO RESPIMAT should be used with caution in patients with urinary retention. Prescribers and patients should be alert for signs and symptoms of prostatic hyperplasia or bladder-neck obstruction (e.g., difficulty passing urine, painful urination), especially in patients with prostatic hyperplasia or bladder neck obstruction. Instruct patients to consult a physician immediately should any of these signs or symptoms develop.

5.10 Renal Impairment

Because tiotropium is a predominantly renally excreted drug, patients with moderate to severe renal impairment (creatinine clearance of <60 mL/min) treated with STIOLTO RESPIMAT should be monitored closely for anticholinergic side effects [see Use in Specific Populations (8.7) and Clinical Pharmacology (12.3)].

5.11 Hypokalemia and Hyperglycemia

Beta-adrenergic agonists may produce significant hypokalemia in some patients, which has the potential to produce adverse cardiovascular effects [see Clinical Pharmacology (12.2)]. The decrease in serum potassium is usually transient, not requiring supplementation. Inhalation of high doses of beta2-adrenergic agonists may produce increases in plasma glucose.

In patients with severe COPD, hypokalemia may be potentiated by hypoxia and concomitant treatment [see Drug Interactions (7.2)], which may increase the susceptibility for cardiac arrhythmias.

Clinically notable decreases in serum potassium or changes in blood glucose were infrequent during clinical studies with long-term administration of olodaterol with the rates similar to those for placebo controls. Olodaterol has not been investigated in patients whose diabetes mellitus is not well controlled.

6 ADVERSE REACTIONS

LABA, such as olodaterol, one of the active components in STIOLTO RESPIMAT, as monotherapy (without an inhaled corticosteroid) for asthma, increase the risk of asthma-related events. STIOLTO RESPIMAT is not indicated for the treatment of asthma [see Warning and Precautions (5.1)].

The following adverse reactions are described, or described in greater detail, in other sections:

- Immediate hypersensitivity reactions [see Warnings and Precautions (5.4)]
- Paradoxical bronchospasm [see Warnings and Precautions (5.5)]
- Worsening of narrow-angle glaucoma [see Warnings and Precautions (5.8)]
- Worsening of urinary retention [see Warnings and Precautions (5.9)]

6.1 Clinical Trials Experience in Chronic Obstructive Pulmonary Disease

Because clinical trials are conducted under widely varying conditions, the incidence of adverse reactions observed in the clinical trials of a drug cannot be directly compared to the incidences in the clinical trials of another drug and may not reflect the incidences observed in practice.

The clinical program for STIOLTO RESPIMAT included 7,151 subjects with COPD in two 52-week active-controlled trials, one 12-week placebo-controlled trial, three 6-week placebo-controlled cross-over trials, and four additional trials of shorter duration. A total of 1,988 subjects received at least 1 dose of STIOLTO RESPIMAT. Adverse reactions observed in the ≤12-week trials were consistent with those observed in the 52-week trials, which formed the primary safety database.

The primary safety database consisted of pooled data from the two 52-week double-blind, active-controlled, parallel group confirmatory clinical trials (Trials 1 and 2). These trials included 5,162 adult COPD patients (72.9% males and 27.1% females) 40 years of age and older. Of these patients, 1,029 were treated with STIOLTO RESPIMAT once daily. The STIOLTO RESPIMAT group was composed of mostly Caucasians (71.1%) with a mean age of 63.8 years and a mean percent predicted FEV1 at baseline of 43.2%. In these two trials, tiotropium 5 mcg and olodaterol 5 mcg were included as active control arms and no placebo was used.

In these two clinical trials, 74% of patients exposed to STIOLTO RESPIMAT reported an adverse reaction compared to 76.6% and 73.3% in the olodaterol 5 mcg and tiotropium 5 mcg groups, respectively. The proportion of patients who discontinued due to an adverse reaction was 7.4% for STIOLTO RESPIMAT treated patients compared to 9.9% and 9.0% for olodaterol 5 mcg and tiotropium 5 mcg treated patients. The adverse reaction most commonly leading to discontinuation was worsening COPD.

The most common serious adverse reactions were COPD exacerbation and pneumonia.

Table 1 shows all adverse drug reactions that occurred with an incidence of >3% in the STIOLTO RESPIMAT treatment group and a higher incidence rate than the active comparator groups listed.

Table 1 Number and frequency of adverse drug reactions greater than 3% (and higher than any of the comparators tiotropium and/or olodaterol) in COPD patients exposed to STIOLTO RESPIMAT: Pooled data from the two 52-week, double-blind, active-controlled clinical trials in COPD patients 40 years of age and older
Treatment | STIOLTO RESPIMAT (once daily) | Tiotropium (5 mcg once daily) | Olodaterol (5 mcg once daily)
Body system (adverse drug reaction) | n=1,029 n (%) | n=1,033 n (%) | n=1,038 n (%)
Infections and infestations
Nasopharyngitis | 128 (12.4) | 121 (11.7) | 131 (12.6)
Respiratory, thoracic, and mediastinal disorders
Cough | 40 (3.9) | 45 (4.4) | 31 (3.0)
Musculoskeletal and connective tissue disorders
Back Pain | 37 (3.6) | 19 (1.8) | 35 (3.4)

Other adverse drug reactions in patients receiving STIOLTO RESPIMAT that occurred in ≤3% of patients in clinical studies are listed below:

Metabolism and nutrition disorders: dehydration
Nervous system disorders: dizziness, insomnia
Eye disorders: glaucoma, intraocular pressure increased, vision blurred
Cardiac/vascular disorders: atrial fibrillation, palpitations, supraventricular tachycardia, tachycardia, hypertension
Respiratory, thoracic, and mediastinal disorders: epistaxis, pharyngitis, dysphonia, bronchospasm, laryngitis, sinusitis
Gastrointestinal disorders: dry mouth, constipation, oropharyngeal candidiasis, dysphagia, gastroesophageal reflux disease, gingivitis, glossitis, stomatitis, intestinal obstruction including ileus paralytic
Skin and subcutaneous disorders: rash, pruritus, angioneurotic edema, urticaria, skin infection, and skin ulcer, dry skin, hypersensitivity (including immediate reactions)
Musculoskeletal and connective tissue disorders: arthralgia, joint swelling
Renal and urinary disorders: urinary retention, dysuria, and urinary tract infection

COPD Exacerbation Reduction Trial

In a one year trial (Trial 5) of 7,880 patients to compare rates of COPD exacerbations, 3,939 patients were treated with STIOLTO RESPIMAT and 3,941 patients were treated with tiotropium 5 mcg inhalation spray. The safety profile of STIOLTO RESPIMAT was similar to that of tiotropium 5 mcg inhalation spray and consistent with that documented in the STIOLTO RESPIMAT primary safety database.

7 DRUG INTERACTIONS

7.1 Adrenergic Drugs

If additional adrenergic drugs are to be administered by any route, they should be used with caution because the sympathetic effects of olodaterol, one component of STIOLTO RESPIMAT, may be potentiated [see Warnings and Precautions (5.3, 5.6, 5.10, 5.11)].

7.2 Sympathomimetics, Xanthine Derivatives, Steroids, or Diuretics

Tiotropium has been used concomitantly with short-acting and long-acting sympathomimetic (beta-agonists) bronchodilators, methylxanthines, and oral and inhaled steroids, without increases in adverse reactions. Concomitant treatment with xanthine derivatives, steroids, or diuretics may potentiate any hypokalemic effect of olodaterol [see Warnings and Precautions (5.11)].

7.3 Non-Potassium Sparing Diuretics

The ECG changes and/or hypokalemia that may result from the administration of non-potassium sparing diuretics (such as loop or thiazide diuretics) can be acutely worsened by beta-agonists, especially when the recommended dosage of the beta-agonist is exceeded. Although the clinical significance of these effects is not known, caution is advised in the co-administration of STIOLTO RESPIMAT with non-potassium sparing diuretics.

7.4 Monoamine Oxidase Inhibitors, Tricyclic Antidepressants, QTc Prolonging Drugs

STIOLTO RESPIMAT, as with other drugs containing beta2-agonists, should be administered with extreme caution to patients being treated with monoamine oxidase inhibitors or tricyclic antidepressants or other drugs known to prolong the QTc interval because the action of adrenergic agonists on the cardiovascular system may be potentiated by these agents. Drugs that are known to prolong the QTc interval may be associated with an increased risk of ventricular arrhythmias.

7.5 Beta-Blockers

Beta-adrenergic receptor antagonists (beta-blockers) and the olodaterol component of STIOLTO RESPIMAT may interfere with the effect of each other when administered concurrently. Beta-blockers not only block the therapeutic effects of beta-agonists, but may produce severe bronchospasm in COPD patients. Therefore, patients with COPD should not normally be treated with beta-blockers. However, under certain circumstances, e.g., as prophylaxis after myocardial infarction, there may be no acceptable alternatives to the use of beta-blockers in patients with COPD. In this setting, cardioselective beta-blockers could be considered, although they should be administered with caution.

7.6 Anticholinergics

There is potential for an additive interaction with concomitantly used anticholinergic medications. Therefore, avoid co-administration of STIOLTO RESPIMAT with other anticholinergic-containing drugs as this may lead to an increase in anticholinergic adverse effects [see Warnings and Precautions (5.8, 5.9) and Adverse Reactions (6)].

7.7 Inhibitors of Cytochrome P450 and P-gp Efflux Transporter

In a drug interaction study using the strong dual CYP and P-gp inhibitor ketoconazole, a 1.7-fold increase of olodaterol maximum plasma concentrations and AUC was observed [see Pharmacokinetics (12.3)]. Olodaterol was evaluated in clinical trials for up to one year at doses up to twice the recommended therapeutic dosage. No dosage adjustment of STIOLTO RESPIMAT is necessary.

8 USE IN SPECIFIC POPULATIONS

8.1 Pregnancy

Risk Summary

There are no adequate and well-controlled clinical studies with STIOLTO RESPIMAT or its individual components, tiotropium bromide and olodaterol, in pregnant women to inform of drug-associated risk of adverse pregnancy-related outcomes. Animal reproduction studies were conducted with the individual components of STIOLTO RESPIMAT, tiotropium bromide and olodaterol. There are clinical considerations with the use of STIOLTO RESPIMAT in pregnant women (see Clinical Considerations). STIOLTO RESPIMAT should be used during pregnancy only if the potential benefit justifies the potential risk to the fetus. Based on animal reproduction studies, no structural abnormalities were observed when tiotropium was administered by inhalation to pregnant rats and rabbits during the period of organogenesis at doses 790 and 8 times, respectively, the maximum recommended human daily inhalation dose (MRHDID). Increased post-implantation loss was observed in rats and rabbits administered tiotropium at maternally toxic doses 430 times and 40 times the MRHDID, respectively (see Data). Based on animal studies, olodaterol was not teratogenic when administered to pregnant rats or rabbits during organogenesis at inhalation doses of approximately 2,731 or 1,353 times the MRHDID (on an AUC basis), in rats or rabbits, respectively (see Data).

The estimated background risk of major birth defects and miscarriage for the indicated population is unknown. All pregnancies have a background risk of birth defect, loss or other adverse outcomes. In the U.S. general population, the estimated background risk of major birth defects and miscarriage in clinically recognized pregnancies is 2% to 4% and 15% to 20%, respectively.

Clinical Considerations

Labor and Delivery

There are no adequate and well-controlled human studies that have investigated the effects of STIOLTO RESPIMAT on preterm labor or labor at term. Because of the potential for beta-agonist interference with uterine contractility, use of STIOLTO RESPIMAT during labor should be restricted to those patients in whom the benefits clearly outweigh the risks.

Data

Animal Data

Animal reproduction studies with the combination of tiotropium and olodaterol are not available; however, studies are available with the individual components.

Tiotropium

In 2 separate embryo-fetal development studies, pregnant rats and rabbits received tiotropium during the period of organogenesis at doses up to approximately 790 and 8 times the MRHDID, respectively (on a mcg/m^2 basis at inhalation doses of 1,471 and 7 mcg/kg/day in rats and rabbits, respectively). No evidence of structural abnormalities was observed in rats or rabbits. However, in rats, tiotropium caused fetal resorption, litter loss, decreases in the number of live pups at birth and the mean pup weights, and a delay in pup sexual maturation at tiotropium doses of approximately 40 times the MRHDID (on a mcg/m^2 basis at a maternal inhalation dose of 78 mcg/kg/day). In rabbits, tiotropium caused an increase in post-implantation loss at a tiotropium dose of approximately 430 times the MRHDID (on a mcg/m^2 basis at a maternal inhalation dose of 400 mcg/kg/day). Such effects were not observed at approximately 5 and 95 times the MRHDID, respectively (on a mcg/m^2 basis at inhalation doses of 9 and 88 mcg/kg/day in rats and rabbits, respectively).

Olodaterol

Olodaterol was not teratogenic in rats at inhalation doses approximately 2,731 times the MRHDID (on an AUC basis at a maternal inhalation dose of 1,054 mcg/kg/day). No significant effects occurred in rabbits at inhalation doses approximately 1,353 times the MRHDID in adults (on an AUC basis at a maternal inhalation dose of 974 mcg/kg/day). Placental transfer of olodaterol was observed in pregnant rats.

Olodaterol has been shown to be teratogenic in New Zealand rabbits at inhalation doses approximately 7,130 times the MRHDID in adults (on an AUC basis at a maternal inhalation dose of 2,489 mcg/kg/day). Olodaterol exhibited the following fetal toxicities: enlarged or small heart atria or ventricles, eye abnormalities, and split or distorted sternum.

8.2 Lactation

Risk Summary

There are no data on the presence of tiotropium or olodaterol in human milk, the effects on the breastfed infant, or the effects on milk production. Tiotropium, olodaterol, and/or their metabolites are present in the milk of lactating rats, however, due to species-specific differences in lactation physiology, the clinical relevance of these data are not clear (see Data). The developmental and health benefits of breastfeeding should be considered along with the mother's clinical need for STIOLTO RESPIMAT and any potential adverse effects on the breastfed child from STIOLTO RESPIMAT or from the underlying maternal condition.

Data

The distributions of tiotropium bromide or olodaterol into milk were investigated in separate studies after a single intravenous administration of 10 mg/kg or 0.4 μmol/kg, respectively, to lactating rats. Tiotropium, olodaterol, and/or their metabolites are present in the milk of lactating rats at concentrations above those in plasma.

8.4 Pediatric Use

COPD does not normally occur in children. The safety and effectiveness of STIOLTO RESPIMAT in the pediatric population has not been established.

8.5 Geriatric Use

Based on available data, no adjustment of STIOLTO RESPIMAT dosage in geriatric patients is warranted [see Clinical Pharmacology (12.3)].

Of the 1,029 patients who received STIOLTO RESPIMAT at the recommended dose once daily in the clinical studies from the pooled 1-year database, 525 (51.0%) were <65 years of age, 407 (39.6%) were 65 to <75, 96 (9.3%) were 75 to <85, and 1 (0.1%) was ≥85.

No overall differences in effectiveness were observed, and in the 1-year pooled data, the adverse drug reaction profiles were similar in the older population compared to the patient population overall.

8.6 Hepatic Impairment

No dose adjustment is needed in patients with mild and moderate hepatic impairment. A study in subjects with severe hepatic impairment was not performed [see Clinical Pharmacology (12.3)].

8.7 Renal Impairment

No dose adjustment is required for patients with renal impairment. However, patients with moderate to severe renal impairment (creatinine clearance of <60 mL/min) treated with STIOLTO RESPIMAT should be monitored closely for anticholinergic side effects [see Dosage and Administration (2), Warnings and Precautions (5.10), and Clinical Pharmacology (12.3)].

10 OVERDOSAGE

STIOLTO RESPIMAT contains both tiotropium bromide and olodaterol; therefore, the risks associated with overdosage for the individual components described below apply to STIOLTO RESPIMAT.

Tiotropium

High doses of tiotropium may lead to anticholinergic signs and symptoms. However, there were no systemic anticholinergic adverse effects following a single inhaled dose of up to 282 mcg tiotropium in 6 healthy volunteers. In a study of 12 healthy volunteers, bilateral conjunctivitis and dry mouth were seen following repeated once-daily inhalation of 141 mcg of tiotropium. Dry mouth/throat and dry nasal mucosa occurred in a dose-dependent [10-40 mcg daily] manner, were observed following 14-day dosing of up to 40 mcg tiotropium bromide inhalation solution in healthy subjects.

Olodaterol

The expected signs and symptoms with overdosage of olodaterol are those of excessive beta-adrenergic stimulation and occurrence or exaggeration of any of the signs and symptoms, e.g., myocardial ischemia, angina pectoris, hypertension or hypotension, tachycardia, arrhythmias, palpitations, dizziness, nervousness, insomnia, anxiety, headache, tremor, dry mouth, muscle spasms, nausea, fatigue, malaise, hypokalemia, hyperglycemia, and metabolic acidosis. As with all inhaled sympathomimetic medications, cardiac arrest and even death may be associated with an overdose of olodaterol.

Treatment of overdosage consists of discontinuation of STIOLTO RESPIMAT together with institution of appropriate symptomatic and supportive therapy. The judicious use of a cardioselective beta-receptor blocker may be considered, bearing in mind that such medication can produce bronchospasm. There is insufficient evidence to determine if dialysis is beneficial for overdosage of STIOLTO RESPIMAT. Cardiac monitoring is recommended in cases of overdosage.

11 DESCRIPTION

STIOLTO RESPIMAT is a combination of tiotropium, an anticholinergic, and olodaterol, a long-acting beta2-adrenergic agonist (LABA).

The drug substance tiotropium bromide monohydrate is chemically described as (1α, 2ß, 4ß, 5α, 7ß)-7-[(Hydroxydi-2-thienylacetyl)oxy]-9,9-dimethyl-3-oxa-9-azoniatricyclo[3.3.1.0^2,4] nonane bromide monohydrate. It is a synthetic, non-chiral, quaternary ammonium compound. Tiotropium bromide is a white or yellowish white powder. It is sparingly soluble in water and soluble in methanol.

The structural formula is:

Tiotropium bromide (monohydrate) has a molecular mass of 490.4 and a molecular formula of C19H22NO4S2Br ∙ H2O.

The drug substance olodaterol hydrochloride is chemically described as 2H-1,4-Benzoxazin-3H(4H)-one, 6-hydroxy-8-[(1R)-1-hydroxy-2-[[2-(4-methoxyphenyl)-1,1-dimethylethyl]-amino]ethyl]-, monohydrochloride. Olodaterol hydrochloride is a white to off-white powder that is sparingly-slightly soluble in water and slightly soluble in ethanol. The molecular weight is 422.9 g/mole (salt): 386.5 g/mole (base), and the molecular formula is C21H26N2O5 × HCl as a hydrochloride. The conversion factor from salt to free base is 1.094.

The structural formula is:

The drug product, STIOLTO RESPIMAT, is composed of a sterile aqueous solution of tiotropium bromide and olodaterol hydrochloride filled into a 4.5 mL plastic container crimped into an aluminum cylinder (STIOLTO RESPIMAT cartridge) for use with the STIOLTO RESPIMAT inhaler.

Excipients include, benzalkonium chloride, edetate disodium, hydrochloric acid, and water for injection.

The STIOLTO RESPIMAT cartridge is only intended for use with the STIOLTO RESPIMAT inhaler. The STIOLTO RESPIMAT inhaler is a hand held, pocket sized oral inhalation device that uses mechanical energy to generate a slow-moving aerosol cloud of medication from a metered volume of the drug solution. The STIOLTO RESPIMAT inhaler has a light green-colored cap.

When used with the STIOLTO RESPIMAT inhaler each cartridge, containing 4 grams of sterile aqueous solution, delivers the labeled number of metered actuations after preparation for use. Each dose (one dose equals two actuations) from the STIOLTO RESPIMAT inhaler delivers 5 mcg tiotropium (equivalent to 6.247 mcg tiotropium bromide monohydrate) and 5 mcg olodaterol (equivalent to 5.473 mcg olodaterol hydrochloride) in 22.1 mcL from the mouthpiece. As with all inhaled drugs, the actual amount of drug delivered to the lung may depend on patient factors, such as the coordination between the actuation of the inhaler and inspiration through the delivery system. The duration of inspiration should be at least as long as the spray duration (1.5 seconds).

12 CLINICAL PHARMACOLOGY

12.1 Mechanism of Action

STIOLTO RESPIMAT

STIOLTO RESPIMAT contains both tiotropium and olodaterol. The properties described below for the individual components apply to STIOLTO RESPIMAT. These drugs represent 2 different classes of medication (an anticholinergic and a beta-agonist) that have different effects on clinical and physiological indices.

Tiotropium

Tiotropium is a long-acting, muscarinic antagonist which is often referred to as an anticholinergic. It has similar affinity to the subtypes of muscarinic receptors, M1 to M5. In the airways, it exhibits pharmacological effects through inhibition of M3-receptors at the smooth muscle leading to bronchodilation. The competitive and reversible nature of antagonism was shown with human and animal origin receptors and isolated organ preparations. In preclinical in vitro as well as in vivo studies, prevention of methacholine-induced bronchoconstriction effects was dose-dependent and lasted longer than 24 hours. The bronchodilation following inhalation of tiotropium is predominantly a site-specific effect.

Olodaterol

Olodaterol is a long-acting beta2-adrenergic agonist (LABA). The compound exerts its pharmacological effects by binding and activation of beta2-adrenoceptors after topical administration by inhalation. Activation of these receptors in the airways results in a stimulation of intracellular adenyl cyclase, an enzyme that mediates the synthesis of cyclic-3', 5' adenosine monophosphate (cAMP). Elevated levels of cAMP induce bronchodilation by relaxation of airway smooth muscle cells. In vitro studies have shown that olodaterol has 241-fold greater agonist activity at beta2-adrenoceptors compared to beta1-adrenoceptors and 2,299-fold greater agonist activity compared to beta3-adrenoceptors. The clinical significance of these findings is unknown.

Beta-adrenoceptors are divided into three subtypes: beta1-adrenoceptors predominantly expressed on cardiac muscle, beta2-adrenoceptors predominantly expressed on airway smooth muscle, and beta3-adrenoceptors predominantly expressed on adipose tissue. Beta2-agonists cause bronchodilation. Although the beta2-adrenoceptor is the predominant adrenergic receptor in the airway smooth muscle, it is also present on the surface of a variety of other cells, including lung epithelial and endothelial cells and in the heart. The precise function of beta2-receptors in the heart is not known, but their presence raises the possibility that even highly selective beta2-agonists may have cardiac effects.

12.2 Pharmacodynamics

Cardiac Electrophysiology

STIOLTO RESPIMAT

In two 52-week randomized, double-blind trials using STIOLTO RESPIMAT that enrolled 5,162 patients with COPD, ECG assessments were performed post-dose on days 1, 85, 169, and 365. In a pooled analysis the number of subjects with changes from baseline-corrected QT interval of >30 msec using both the Bazett (QTcB) and Fredericia (QTcF), corrections of QT for heart rate were not different for the STIOLTO RESPIMAT group compared to olodaterol 5 mcg and tiotropium 5 mcg across the assessments conducted.

Tiotropium

The effect of tiotropium dry powder for inhalation on QT interval was also evaluated in a randomized, placebo- and positive-controlled crossover study in 53 healthy volunteers. Subjects received tiotropium inhalation powder 18 mcg, 54 mcg (3 times the recommended dose), or placebo for 12 days. ECG assessments were performed at baseline and throughout the dosing interval following the first and last dose of study medication. Relative to placebo, the maximum mean change from baseline in study-specific QTc interval was 3.2 msec and 0.8 msec for tiotropium inhalation powder 18 mcg and 54 mcg, respectively. No subject showed a new onset of QTc >500 msec or QTc changes from baseline of ≥60 msec.

In a multicenter, randomized, double-blind trial using tiotropium dry powder for inhalation that enrolled 198 patients with COPD, the number of subjects with changes from baseline-corrected QT interval of 30–60 msec was higher in the tiotropium group as compared with placebo. This difference was apparent using both the Bazett (QTcB) [20 (20%) patients vs. 12 (12%) patients] and Fredericia (QTcF) [16 (16%) patients vs. 1 (1%) patient] corrections of QT for heart rate. No patients in either group had either QTcB or QTcF of >500 msec. Other clinical trials with tiotropium did not detect an effect of the drug on QTc intervals.

Olodaterol

The effect of olodaterol on the QT/QTc interval of the ECG was investigated in 24 healthy male and female volunteers in a double-blind, randomized, placebo- and active (moxifloxacin)- controlled study at single doses of 10, 20, 30, and 50 mcg. Dose-dependent QtcI (individual subject corrected QT interval) prolongation was observed. The maximum mean (one-sided 95% upper confidence bound) difference in QTcI from placebo after baseline correction was 2.5 (5.6) ms, 6.1 (9.2) ms, 7.5 (10.7) ms, and 8.5 (11.6) ms following doses of 10, 20, 30, and 50 mcg, respectively.

The effect of 5 mcg and 10 mcg olodaterol on heart rate and rhythm was assessed using continuous 24-hour ECG recording (Holter monitoring) in a subset of 772 patients in the 48-week, placebo-controlled phase 3 trials. There were no dose- or time-related trends or patterns observed for the magnitudes of mean changes in heart rate or premature beats. Shifts from baseline to the end of treatment in premature beats did not indicate meaningful differences between olodaterol 5 mcg, 10 mcg, and placebo.

12.3 Pharmacokinetics

STIOLTO RESPIMAT

When STIOLTO RESPIMAT was administered by the inhalation route, the pharmacokinetic parameters for tiotropium and for olodaterol were similar to those observed when each active substance was administered separately.

Tiotropium

Tiotropium is administered as an inhalation spray. Some of the pharmacokinetic data described below were obtained with higher doses than recommended for therapy.

Olodaterol

Olodaterol showed linear pharmacokinetics. On repeated once-daily inhalation, steady-state of olodaterol plasma concentrations was achieved after 8 days, and the extent of exposure was increased up to 1.8-fold as compared to a single dose.

Absorption

Tiotropium

Following inhalation of the solution by young healthy volunteers, urinary excretion data suggests that approximately 33% of the inhaled dose reaches the systemic circulation. Oral solutions of tiotropium have an absolute bioavailability of 2% to 3%. Food is not expected to influence the absorption of tiotropium for the same reason. Maximum tiotropium plasma concentrations were observed 5 to 7 minutes after inhalation.

Olodaterol

Olodaterol reaches maximum plasma concentrations generally within 10 to 20 minutes following drug inhalation. In healthy volunteers the absolute bioavailability of olodaterol following inhalation was estimated to be approximately 30%, whereas the absolute bioavailability was below 1% when given as an oral solution. Thus, the systemic availability of olodaterol after inhalation is mainly determined by lung absorption, while any swallowed portion of the dose only negligibly contributes to systemic exposure.

Distribution

Tiotropium

The drug has a plasma protein binding of 72% and shows a volume of distribution of 32 L/kg. Local concentrations in the lung are not known, but the mode of administration suggests substantially higher concentrations in the lung. Studies in rats have shown that tiotropium does not penetrate the blood-brain barrier.

Olodaterol

Olodaterol exhibits multi-compartmental disposition kinetics after inhalation as well as after intravenous administration. The volume of distribution is high (1,110 L), suggesting extensive distribution into tissue. In vitro binding of [^14C] olodaterol to human plasma proteins is independent of concentration and is approximately 60%.

Elimination

Metabolism

Tiotropium

The extent of metabolism is small. This is evident from a urinary excretion of 74% of unchanged substance after an intravenous dose to young healthy volunteers. Tiotropium, an ester, is nonenzymatically cleaved to the alcohol N-methylscopine and dithienylglycolic acid, both not binding to muscarinic receptors.

In vitro experiments with human liver microsomes and human hepatocytes suggest that a fraction of the administered dose (74% of an intravenous dose is excreted unchanged in the urine, leaving 25% for metabolism) is metabolized by cytochrome P450-dependent oxidation and subsequent glutathione conjugation to a variety of Phase 2 metabolites. This enzymatic pathway can be inhibited by CYP450 2D6 and 3A4 inhibitors, such as quinidine, ketoconazole, and gestodene. Thus, CYP450 2D6 and 3A4 are involved in the metabolic pathway that is responsible for the elimination of a small part of the administered dose. In vitro studies using human liver microsomes showed that tiotropium in supra-therapeutic concentrations does not inhibit CYP450 1A1, 1A2, 2B6, 2C9, 2C19, 2D6, 2E1, or 3A4.

Olodaterol

Olodaterol is substantially metabolized by direct glucuronidation and by O-demethylation at the methoxy moiety followed by conjugation. Of the six metabolites identified, only the unconjugated demethylation product binds to beta2-receptors. This metabolite, however, is not detectable in plasma after chronic inhalation of the recommended therapeutic dose.

Cytochrome P450 isozymes CYP2C9 and CYP2C8, with negligible contribution of CYP3A4, are involved in the O-demethylation of olodaterol, while uridine diphosphate glycosyl transferase isoforms UGT2B7, UGT1A1, 1A7, and 1A9 were shown to be involved in the formation of olodaterol glucuronides.

Excretion

Tiotropium

The terminal half-life of tiotropium in COPD patients following once daily inhalation of 5 mcg tiotropium was approximately 25 hours. Total clearance was 880 mL/min after an intravenous dose in young healthy volunteers. Intravenously administered tiotropium bromide is mainly excreted unchanged in urine (74%). After inhalation of the solution by patients with COPD, urinary excretion is 18.6% (0.932 mcg) of the dose, the remainder being mainly non-absorbed drug in the gut that is eliminated via the feces. The renal clearance of tiotropium exceeds the creatinine clearance, indicating secretion into the urine. After chronic once-daily inhalation by COPD patients, pharmacokinetic steady state was reached by day 7 with no accumulation thereafter.

Olodaterol

Total clearance of olodaterol in healthy volunteers is 872 mL/min, and renal clearance is 173 mL/min. The terminal half-life following intravenous administration is 22 hours. The terminal half-life following inhalation in contrast is about 45 hours, indicating that the latter is determined by absorption rather than by elimination processes. However, the effective half-life at daily dose of 5 mcg calculated from Cmax from COPD patients is 7.5 hours.

Following intravenous administration of [^14C]-labeled olodaterol, 38% of the radioactive dose was recovered in the urine and 53% was recovered in feces. The amount of unchanged olodaterol recovered in the urine after intravenous administration was 19%. Following oral administration, only 9% of olodaterol and/or its metabolites was recovered in urine, while the major portion was recovered in feces (84%). More than 90% of the dose was excreted within 6 and 5 days following intravenous and oral administration, respectively. Following inhalation, excretion of unchanged olodaterol in urine within the dosing interval in healthy volunteers at steady state accounted for 5% to 7% of the dose.

Drug Interactions

STIOLTO RESPIMAT

Pharmacokinetic drug interaction studies with STIOLTO RESPIMAT have not been performed; however, such studies have been conducted with individual components tiotropium and olodaterol.

When tiotropium and olodaterol were administered in combination by the inhaled route, the pharmacokinetic parameters for each component were similar to those observed when each active substance was administered separately.

Tiotropium

An interaction study with tiotropium (14.4 mcg intravenous infusion over 15 minutes) and cimetidine 400 mg three times daily or ranitidine 300 mg once-daily was conducted. Concomitant administration of cimetidine with tiotropium resulted in a 20% increase in the AUC0-4h, a 28% decrease in the renal clearance of tiotropium and no significant change in the Cmax and amount excreted in urine over 96 hours. Co-administration of tiotropium with ranitidine did not affect the pharmacokinetics of tiotropium.

Common concomitant medications (long-acting beta2-adrenergic agonists (LABA), inhaled corticosteroids (ICS)) used by patients with COPD were not found to alter the exposure to tiotropium.

Olodaterol

Drug-drug interaction studies were carried out using fluconazole as a model inhibitor of CYP 2C9 and ketoconazole as a potent P-gp (and CYP3A4, 2C8, 2C9) inhibitor.

Fluconazole: Co-administration of 400 mg fluconazole once a day for 14 days had no relevant effect on systemic exposure to olodaterol.

Ketoconazole: Co-administration of 400 mg ketoconazole once a day for 14 days increased olodaterol Cmax by 66% and AUC0-1 by 68%.

Tiotropium: Co-administration of tiotropium bromide, delivered as a fixed-dose combination with olodaterol, for 21 days had no relevant effect on systemic exposure to olodaterol, and vice versa.

Specific Populations

Olodaterol

A pharmacokinetic meta-analysis showed that no dose adjustment is necessary based on the effect of age, gender, and weight on systemic exposure in COPD patients after inhalation of olodaterol.

Geriatric Patients

Tiotropium:

As expected for all predominantly renally excreted drugs, advancing age was associated with a decrease of tiotropium renal clearance (347 mL/min in COPD patients <65 years to 275 mL/min in COPD patients ≥65 years). This did not result in a corresponding increase in AUC0-6,ss and Cmax,ss values.

Renal Impairment

Tiotropium

Following inhaled administration of therapeutic doses of tiotropium to steady-state to patients with COPD, mild renal impairment (creatinine clearance 60 - <90 mL/min) resulted in 23% higher AUC0-6,ss and 17% higher Cmax,ss values. Moderate renal impairment (creatinine clearance 30 - <60 mL/min) resulted in 57% higher AUC0-6,ss and 31% higher Cmax,ss values compared to COPD patients with normal renal function (creatinine clearance ≥90 mL/min). In COPD patients with severe renal impairment (CLCR <30 mL/min), a single intravenous administration of tiotropium bromide resulted in 94% higher AUC0-4 and 52% higher Cmax compared to COPD patients with normal renal function.

Olodaterol

Olodaterol levels were increased by approximately 40% in subjects with severe renal impairment. A study in subjects with mild and moderate renal impairment was not performed.

Hepatic Impairment

Tiotropium

The effects of hepatic impairment on the pharmacokinetics of tiotropium were not studied.

Olodaterol

Subjects with mild and moderate hepatic impairment showed no changes in Cmax or AUC, nor did protein binding differ between mild and moderate hepatically impaired subjects and their healthy controls. A study in subjects with severe hepatic impairment was not performed.

13 NONCLINICAL TOXICOLOGY

13.1 Carcinogenesis, Mutagenesis, Impairment of Fertility

STIOLTO RESPIMAT

No studies of the carcinogenicity, in vitro mutagenicity, or impairment of fertility were conducted with STIOLTO RESPIMAT, however, studies are available for the individual components, tiotropium and olodaterol.

Tiotropium

No evidence of tumorigenicity was observed in a 104-week inhalation study in rats at tiotropium doses up to 59 mcg/kg/day, in an 83-week inhalation study in female mice at doses up to 145 mcg/kg/day, and in a 101-week inhalation study in male mice at doses up to 2 mcg/kg/day. These doses correspond to approximately 30, 40, and 0.5 times the recommended human daily inhalation dose (RHDID) on a mcg/m^2 basis, respectively.

Tiotropium bromide demonstrated no evidence of mutagenicity or clastogenicity in the following assays: the bacterial gene mutation assay, the V79 Chinese hamster cell mutagenesis assay, the chromosomal aberration assay in human lymphocytes in vitro, the mouse micronucleus assay in vivo, and the unscheduled DNA synthesis assay in primary rat hepatocytes in vitro.

In rats, decreases in the number of corpora lutea and the percentage of implants were noted at inhalation tiotropium doses of 78 mcg/kg/day or greater (approximately 35 times the RHDID on a mcg/m^2 basis). No such effects were observed at 9 mcg/kg/day (approximately 4 times than the RHDID on a mcg/m^2 basis). The fertility index; however, was not affected at inhalation doses up to 1,689 mg/kg/day (approximately 760 times the RHDID on a mcg/m^2 basis).

Olodaterol

Two-year inhalation studies were conducted in rats and mice to assess the carcinogenic potential of olodaterol. Lifetime treatment of female rats induced leiomyomas of the mesovarium at doses of 25.8 and 270 mcg/kg/day (approximately 18- and 198-fold, respectively, the RHDID on an AUC basis). No tumor findings were observed in male rats at doses up to 270 mcg/kg/day (approximately 230-fold the RHDID on an AUC basis). Lifetime treatment of female mice induced leiomyomas and leiomyosarcomas of the uterus at doses ≥76.9 mcg/kg/day (approximately 106-fold the RHDID on an AUC basis). No tumor findings were observed in male mice at doses up to 255 mcg/kg/day (approximately 455-fold the RHDID on an AUC basis). Increases in leiomyomas and leiomyosarcomas of the female rodent reproductive tract have been similarly demonstrated with other beta2-adrenergic agonist drugs. The relevance of these findings to human use is unknown.

Olodaterol was not mutagenic in the in vitro Ames test or in the in vitro mouse lymphoma assay. Olodaterol produced increased frequency of micronuclei in rats after intravenous doses. The increased frequency of micronuclei was likely related to drug enhanced (compensatory) erythropoiesis. The mechanism for induction of micronuclei formation is likely not relevant at clinical exposures.

Olodaterol did not impair male or female fertility in rats at inhalation doses up to 3,068 mcg/kg/day (approximately 2,322 times the RHDID on an AUC basis).

14 CLINICAL STUDIES

The safety and efficacy of STIOLTO RESPIMAT were evaluated in a clinical development program that included three dose ranging trials, two active-controlled trials, three active- and placebo-controlled trials, and one placebo-controlled trial. The efficacy of STIOLTO RESPIMAT is based primarily on two 4-week dose-ranging trials in 592 COPD patients and two confirmatory active-controlled 52-week trials (Trials 1 and 2) in 5,162 COPD patients.

Dose-Ranging Trials

Dose selection for STIOLTO RESPIMAT was primarily based on trials for the individual components, tiotropium bromide and olodaterol.

Dose selection was also supported by two randomized, double-blind, active-controlled, 4-week trials. In one trial in 232 patients with COPD, three tiotropium doses (1.25, 2.5, and 5 mcg) were given in combination with olodaterol 5 or 10 mcg and were evaluated compared to olodaterol monotherapy. Results demonstrated improvement in trough FEV1 for the combination when compared to olodaterol alone. The difference in trough FEV1 for the tiotropium bromide/olodaterol doses of 1.25/5, 2.5/5, and 5/5 mcg once daily from olodaterol 5 mcg were 0.054 L (95% CI 0.016, 0.092), 0.065 L (0.027, 0.103), and 0.084 L (0.046, 0.122), respectively. In the second trial in 360 patients with COPD, three olodaterol doses (2, 5, and 10 mcg) were given in combination with tiotropium 5 mcg and were evaluated compared to tiotropium monotherapy. The difference in trough FEV1 for the tiotropium/olodaterol doses of 5/2, 5/5, and 5/10 mcg once daily from tiotropium 5 mcg were 0.024 L (95% CI -0.029, 0.076), 0.033 L (-0.019, 0.085), and 0.057 L (0.004, 0.110), respectively. Results of these trials supported the evaluation of once-daily doses of tiotropium bromide/olodaterol 2.5/5 mcg and 5/5 mcg in the confirmatory trials.

Confirmatory Trials

A total of 5,162 COPD patients (1,029 receiving STIOLTO RESPIMAT, 1,038 receiving olodaterol 5 mcg, and 1,033 receiving tiotropium bromide 5 mcg) were studied in two confirmatory trials of STIOLTO RESPIMAT. Trials 1 and 2 were 52-week, replicate, randomized, double-blind, active controlled, parallel group trials that compared STIOLTO RESPIMAT to tiotropium 5 mcg and olodaterol 5 mcg. In these trials, all products were administered via the RESPIMAT inhaler.

The trials enrolled patients 40 years of age or older with a clinical diagnosis of COPD, a smoking history of more than 10 pack-years, and moderate to very severe pulmonary impairment (post-bronchodilator FEV1 less than 80% predicted normal [GOLD Stage 2-4]; post-bronchodilator FEV1 to FVC ratio of less than 70%). All treatments were administered once daily in the morning. The primary endpoints were change from baseline in FEV1 AUC0-3hr and trough FEV1 after 24 weeks of treatment.

The majority of the 5162 patients were male (73%), white (71%) or Asian (25%), with a mean age of 64.0 years. Mean post-bronchodilator FEV1 was 1.37 L (GOLD 2 [50%], GOLD 3 [39%], GOLD 4 [11%]). Mean beta2-agonist responsiveness was 16.6% of baseline (0.171 L). Pulmonary medications allowed as concomitant therapy included inhaled steroids [47%] and xanthines [10%].

In both Trials 1 and 2, STIOLTO RESPIMAT demonstrated significant improvements in FEV1 AUC0-3hr and trough FEV1 after 24 weeks compared to tiotropium 5 mcg and olodaterol 5 mcg (Table 2). The increased bronchodilator effects of STIOLTO RESPIMAT compared to tiotropium 5 mcg and olodaterol 5 mcg were maintained throughout the 52-week treatment period. STIOLTO RESPIMAT displayed a mean increase in FEV1 from baseline of 0.137 L (range: 0.133-0.140 L) within 5 minutes after the first dose. Patients treated with STIOLTO RESPIMAT used less rescue medication compared to patients treated with tiotropium 5 mcg and olodaterol 5 mcg.

Table 2 FEV1 AUC0-3hr and Trough FEV1 response for STIOLTO RESPIMAT compared to tiotropium 5 mcg and olodaterol 5 mcg after 24 weeks (primary endpoints; Trials 1 and 2)
 | Trial 1 |  |  | Trial 2
 | n | Mean (L) | Difference (L) (95% CI) | n | Mean (L) | Difference (L) (95% CI)
FEV1 AUC0-3hr response
STIOLTO RESPIMAT | 522 | 0.256 | - | 502 | 0.268 | -
Tiotropium 5 mcg | 526 | 0.139 | 0.117 (0.094, 0.140) | 500 | 0.165 | 0.103 (0.078, 0.127)
Olodaterol 5 mcg | 525 | 0.133 | 0.123 (0.100, 0.146) | 507 | 0.136 | 0.132 (0.108, 0.157)
Trough FEV1 response
STIOLTO RESPIMAT | 521 | 0.136 | - | 497 | 0.145 | -
Tiotropium 5 mcg | 520 | 0.065 | 0.071 (0.047, 0.094) | 498 | 0.096 | 0.050 (0.024, 0.075)
Olodaterol 5 mcg | 519 | 0.054 | 0.082 (0.059, 0.106) | 503 | 0.057 | 0.088 (0.063, 0.113)
Pre-treatment baseline FEV1: Trial 1=1.16 L; Trial 2=1.15 L
p≤0.0001 for all comparisons between STIOLTO RESPIMAT and the monotherapies.

For the subset of patients (n=521) who completed extended lung function measurements up to 12 hours post-dose, STIOLTO RESPIMAT showed a significantly greater FEV1 response compared to tiotropium 5 mcg and olodaterol 5 mcg over the full 24-hour dosing interval. Results from Trial 2 are shown in Figure 1.

Figure 1 FEV1 profile for STIOLTO RESPIMAT, tiotropium 5 mcg and olodaterol 5 mcg over a 24-hour dosing interval after 24 weeks (12 hr PFT subset from Trial 2)

The St. George's Respiratory Questionnaire (SGRQ) was assessed in Trials 1 and 2 and in two additional 12-week placebo-controlled trials (Trials 3 and 4).

In the first 12-week trial, SGRQ responder rates at week 12 (defined as an improvement in score of 4 or more as a threshold) were 53%, 42%, and 31% for STIOLTO RESPIMAT, tiotropium 5 mcg, and placebo, respectively, with odds ratios of 1.6 (95% CI 1.1, 2.4) and 2.5 (95% CI 1.6, 3.8) for STIOLTO RESPIMAT vs. tiotropium 5 mcg and STIOLTO RESPIMAT vs. placebo, respectively. In the second 12-week trial, results were similar with odds ratios of 1.5 (95% CI 1.0, 2.3) and 2.2 (95% CI 1.5, 3.4) for STIOLTO RESPIMAT vs. tiotropium 5 mcg and STIOLTO RESPIMAT vs. placebo, respectively. For the 52-week trials similar responder rates were seen. In Trial 1, the odds ratios for STIOLTO vs. tiotropium 5 mcg and STIOLTO vs. olodaterol 5 mcg at week 24 were 1.6 (95% CI 1.2, 2.0) and 1.9 (95% CI 1.5, 2.4), respectively. The results were similar in the 52-week Trial 2, with odds ratios for STIOLTO vs. tiotropium 5 mcg and STIOLTO vs. olodaterol 5 mcg of 1.3 (95% CI 1.0, 1.7) and 1.5 (95% CI 1.1, 1.9), respectively.

Exacerbations

Tiotropium 5 mcg Trials Evaluating Exacerbations

The effect of tiotropium 5 mcg inhalation spray on exacerbations was evaluated in three 48-week randomized, double-blind, placebo-controlled clinical trials that included COPD exacerbations as the primary endpoint. Exacerbations of COPD were defined as a complex of lower respiratory events/symptoms (increase or new onset) related to the underlying COPD, with duration of three days or more, requiring a prescription of antibiotics and/or systemic steroids and/or hospitalization. In a pooled analysis of the first two trials, tiotropium 5 mcg significantly reduced the number of COPD exacerbations compared to placebo with a rate ratio of 0.78 (95% CI 0.67, 0.92). In the third trial, tiotropium 5 mcg delayed the time to first COPD exacerbation compared to placebo with a hazard ratio of 0.69 (95% CI 0.63, 0.77).

STIOLTO RESPIMAT Trial Evaluating Exacerbations

In a one-year, randomized, double-blind, active-controlled parallel group clinical trial (Trial 5), the effect of STIOLTO RESPIMAT on COPD exacerbations was compared with tiotropium 5 mcg inhalation spray. Exacerbations were defined as above. Enrolled patients (3,939 patients receiving STIOLTO RESPIMAT and 3,941 patients receiving tiotropium 5 mcg inhalation spray) had a history of COPD exacerbation in the previous 12 months. The primary endpoint was the annualized rate of moderate to severe COPD exacerbations. The majority of patients were male (71%) and Caucasian (79%). The mean age was 66 years, and mean post-bronchodilator FEV1 percent predicted was 45%. STIOLTO RESPIMAT treatment did not demonstrate superiority to tiotropium 5 mcg inhalation spray for the primary endpoint, the annualized rate of moderate to severe COPD exacerbations, with a rate ratio of 0.93 (99% CI, 0.85-1.02, p=0.0498). The study did not reach the pre-specified significance level of 0.01.

16 HOW SUPPLIED/STORAGE AND HANDLING

STIOLTO RESPIMAT Inhalation Spray is supplied in a labeled carton containing one STIOLTO RESPIMAT cartridge and one STIOLTO RESPIMAT inhaler.

The STIOLTO RESPIMAT cartridge is provided as an aluminum cylinder with a tamper protection seal on the cap. The STIOLTO RESPIMAT cartridge is only intended for use with the STIOLTO RESPIMAT inhaler and should not be interchanged with any other RESPIMAT device delivered product.

The STIOLTO RESPIMAT inhaler is a cylindrical shaped plastic inhalation device with a gray colored body and a clear base. The clear base is removed to insert the cartridge. The inhaler contains a dose indicator. The light green-colored cap and the written information on the label of the gray inhaler body indicate that it is labeled for use with the STIOLTO RESPIMAT cartridge.

STIOLTO RESPIMAT Inhalation Spray is available as:

- STIOLTO RESPIMAT Inhalation Spray: 60 metered actuations (NDC 0597-0155-61)
- STIOLTO RESPIMAT Inhalation Spray: 10 metered actuations (NDC 0597-0155-70) (institutional pack)

The STIOLTO RESPIMAT cartridge has a net fill weight of at least 4 grams and when used with the STIOLTO RESPIMAT inhaler, is designed to deliver the labeled number of metered actuations after preparation for use.

When the labeled number of actuations has been dispensed from the inhaler, the RESPIMAT locking mechanism will be engaged and no more actuations can be dispensed.

After assembly, the STIOLTO RESPIMAT inhaler should be discarded at the latest 3 months after first use or when the locking mechanism is engaged, whichever comes first.

Keep out of reach of children. Do not spray into eyes.

Storage

Store at 20°C to 25°C (68°F to 77°F); excursions permitted to 15°C to 30°C (59°F to 86°F) [see USP Controlled Room Temperature]. Avoid freezing.

17 PATIENT COUNSELING INFORMATION

Advise the patient to read the FDA-approved patient labeling (Patient Information and Instructions for Use).

Serious Asthma-Related Events

Inform patients that LABA, such as STIOLTO RESPIMAT, when used as monotherapy [without an inhaled corticosteroid], increase the risk of serious asthma-related events, including asthma-related death. STIOLTO RESPIMAT is not indicated for the treatment of asthma.

Not for Acute Symptoms

STIOLTO RESPIMAT is not meant to relieve acute asthma symptoms or exacerbations of COPD and extra doses should not be used for that purpose. Acute symptoms should be treated with an inhaled, short-acting beta2-agonist such as albuterol. (The healthcare provider should provide the patient with such medication and instruct the patient in how it should be used.)

Instruct patients to notify their physician immediately if they experience any of the following:

- Worsening of symptoms
- Decreasing effectiveness of inhaled, short-acting beta2-agonists
- Need for more inhalations than usual of inhaled, short-acting beta2-agonists
- Significant decrease in lung function as outlined by the physician

Instruct patients not to stop therapy with STIOLTO RESPIMAT without physician/provider guidance since symptoms may recur after discontinuation.

Do Not Use Additional Long-Acting Beta2-Agonists

Patients who have been taking inhaled, short-acting beta2-agonists on a regular basis should be instructed to discontinue the regular use of these products and use them only for the symptomatic relief of acute symptoms.

When patients are prescribed STIOLTO RESPIMAT, other inhaled medications containing long-acting beta2-agonists should not be used. Patients should not use more than the recommended once-daily dosage of STIOLTO RESPIMAT. Excessive use of sympathomimetics may cause significant cardiovascular effects, and may be fatal.

Risks Associated with Beta2-Agonist Therapy

Inform patients of adverse effects associated with beta2-agonists, such as palpitations, chest pain, rapid heart rate, tremor, or nervousness.

Immediate Hypersensitivity Reactions

Inform patients that anaphylaxis, angioedema (including swelling of the lips, tongue, or throat), urticaria, rash, bronchospasm, or itching, may occur after administration of STIOLTO RESPIMAT. Advise patient to immediately discontinue treatment and consult a physician should any of these signs or symptoms develop.

Paradoxical Bronchospasm

Inform patients that STIOLTO RESPIMAT can produce paradoxical bronchospasm. Advise patients that if paradoxical bronchospasm occurs, patients should discontinue STIOLTO RESPIMAT.

Urinary Retention

Difficulty passing urine and dysuria may be symptoms of new or worsening prostatic hyperplasia or bladder outlet obstruction. Patients should be instructed to consult a physician immediately should any of these signs or symptoms develop.

Visual Effects

Eye pain or discomfort, blurred vision, visual halos or colored images in association with red eyes from conjunctival congestion and corneal edema may be signs of acute narrow-angle glaucoma. Inform patients to consult a physician immediately should any of these signs and symptoms develop. Advise patients that miotic eye drops alone are not considered to be effective treatment.

Inform patients that care must be taken not to allow the aerosol cloud to enter into the eyes as this may cause blurring of vision and pupil dilation.

Since dizziness and blurred vision may occur with the use of STIOLTO RESPIMAT, caution patients about engaging in activities such as driving a vehicle or operating appliances or machinery.

Instructions for Administering STIOLTO RESPIMAT

It is important for patients to understand how to correctly administer STIOLTO RESPIMAT inhalation spray using the STIOLTO RESPIMAT inhaler. Instruct patients that STIOLTO RESPIMAT inhalation spray should only be administered via the STIOLTO RESPIMAT inhaler and the STIOLTO RESPIMAT inhaler should not be used for administering other medications.

Instruct patients that priming STIOLTO RESPIMAT is essential to ensure appropriate content of the medication in each actuation.

When using the unit for the first time, the STIOLTO RESPIMAT cartridge is inserted into the STIOLTO RESPIMAT inhaler and the unit is primed. STIOLTO RESPIMAT patients are to actuate the inhaler toward the ground until an aerosol cloud is visible and then to repeat the process three more times. The unit is then considered primed and ready for use. If not used for more than 3 days, patients are to actuate the inhaler once to prepare the inhaler for use. If not used for more than 21 days, patients are to actuate the inhaler until an aerosol cloud is visible and then repeat the process three more times to prepare the inhaler for use.

Distributed by:
Boehringer Ingelheim Pharmaceuticals, Inc.
Ridgefield, CT 06877 USA

Licensed from:
Boehringer Ingelheim International GmbH

STIOLTO® and RESPIMAT® are registered trademarks of and are used under license from Boehringer Ingelheim International GmbH

Copyright © 2025 Boehringer Ingelheim International GmbH
ALL RIGHTS RESERVED

COL10537BA092025

PATIENT INFORMATION
STIOLTO® RESPIMAT® (sti-OL-to– RES peh mat)
(tiotropium bromide and olodaterol inhalation spray), for oral inhalation use

What is STIOLTO RESPIMAT?

- STIOLTO RESPIMAT combines an anticholinergic, tiotropium bromide and a long-acting beta2-adrenergic agonist (LABA) medicine, olodaterol.
- Anticholinergic and LABA medicines such as STIOLTO RESPIMAT help the muscles around the airways in your lungs stay relaxed to prevent symptoms, such as wheezing, cough, chest tightness, and shortness of breath. These symptoms can happen when the muscles around the airways tighten. This makes it hard to breathe.
- STIOLTO RESPIMAT is a prescription medicine used to control the symptoms of COPD in adults with COPD. COPD is a chronic lung disease that includes chronic bronchitis, emphysema, or both.
- STIOLTO RESPIMAT is for long-term use and should be taken as 2 puffs 1 time each day, to improve the symptoms of COPD for better breathing.
- STIOLTO RESPIMAT is not used to treat sudden symptoms of COPD. Always have a beta2-agonist inhaler medicine (rescue inhaler) with you to treat sudden symptoms of COPD. If you do not have a rescue inhaler, contact your healthcare provider to have one prescribed for you.
- STIOLTO RESPIMAT is not for the treatment of asthma. It is not known if STIOLTO RESPIMAT is safe and effective in people with asthma.
- STIOLTO RESPIMAT should not be used in children. It is not known if STIOLTO RESPIMAT is safe and effective in children.

Do not use STIOLTO RESPIMAT if you:

- have asthma.
- are allergic to tiotropium, ipratropium, olodaterol, or any of the ingredients in STIOLTO RESPIMAT. See the end of this Patient Information leaflet for a complete list of ingredients in STIOLTO RESPIMAT.

Before you use STIOLTO RESPIMAT, tell your healthcare provider about all of your medical conditions, including if you:

- have heart problems.
- have high blood pressure.
- have seizures.
- have thyroid problems.
- have diabetes.
- have eye problems, such as glaucoma. STIOLTO RESPIMAT can make your glaucoma worse.
- have prostate or bladder problems, or problems passing urine. STIOLTO RESPIMAT can make these problems worse.
- have kidney problems.
- are pregnant or plan to become pregnant. It is not known if the medicines tiotropium or olodaterol in STIOLTO RESPIMAT can harm your unborn baby.
- are breastfeeding or plan to breastfeed. It is not known if the medicines tiotropium or olodaterol in STIOLTO RESPIMAT passes into your breast milk and if it can harm your baby. You and your healthcare provider should decide if you will take STIOLTO RESPIMAT while breastfeeding.

Tell your healthcare provider about all the medicines you take, including prescription and over-the-counter medicines, eye drops, vitamins, and herbal supplements. STIOLTO RESPIMAT and certain other medicines may affect each other. This may cause serious side effects.
Especially tell your healthcare provider if you take:

- anticholinergics (including ipratropium, aclidinium, umeclidinium or another tiotropium-containing product such as SPIRIVA RESPIMAT or SPIRIVA HANDIHALER)
- atropine

Know the medicines you take. Keep a list of your medicines with you to show your healthcare provider and pharmacist each time you get a new medicine.

How should I use STIOLTO RESPIMAT?
Read the step-by-step instructions for using STIOLTO RESPIMAT at the end of this Patient Information leaflet.

- Do not use STIOLTO RESPIMAT unless your healthcare provider has taught you how to use the inhaler and you understand how to use it correctly. Ask your healthcare provider or pharmacist if you have any questions.
- STIOLTO RESPIMAT inhaler has a slow-moving mist that helps you inhale the medicine.
- Use STIOLTO RESPIMAT exactly as your healthcare provider tells you to use it. Do not use STIOLTO RESPIMAT more often than prescribed.
- Use 1 dose (2 puffs) of STIOLTO RESPIMAT, 1 time each day, at the same time of the day.
- If you miss a dose of STIOLTO RESPIMAT, take it as soon as you remember. Do not take more than 1 dose (2 puffs) in 24 hours.
- If you take too much STIOLTO RESPIMAT, call your healthcare provider or go to the nearest hospital emergency room right away.
- Do not spray STIOLTO RESPIMAT in your eyes. Your vision may become blurred and your pupils may become larger (dilated).
- STIOLTO RESPIMAT Inhalation Spray should only be given using the STIOLTO RESPIMAT inhaler. The STIOLTO RESPIMAT inhaler should not be used to give other medicines.
- Always use the new STIOLTO RESPIMAT inhaler that is provided with each new prescription.
- STIOLTO RESPIMAT does not relieve sudden symptoms of COPD. You should not take extra doses of STIOLTO RESPIMAT to relieve sudden symptoms of COPD. Always have a rescue inhaler medicine with you to treat sudden symptoms. If you do not have a rescue inhaler medicine, call your healthcare provider to have one prescribed for you.
- If your COPD symptoms worsen over time, do not increase your dose of STIOLTO RESPIMAT, instead call your healthcare provider.
- Do not stop using STIOLTO RESPIMAT or other medicines to control or treat your COPD unless told to do so by your healthcare provider because your symptoms might get worse. Your healthcare provider will change your medicines as needed.
- Do not use STIOLTO RESPIMAT:
  - more often than prescribed for you,
  - at a higher dose than prescribed for you, or
  - with other medicines that contain LABA or an anticholinergic for any reason. Ask your healthcare provider or pharmacist if any of your other medicines are LABA or anticholinergic medicines.
- Call your healthcare provider or get emergency medical care right away if your breathing problems worsen with STIOLTO RESPIMAT, you need to use your rescue inhaler medicine more often than usual, or your rescue inhaler medicine does not work as well for you at relieving your symptoms.

What are the possible side effects with STIOLTO RESPIMAT?
STIOLTO RESPIMAT can cause serious side effects, including:

- serious problems from asthma. People with asthma who take long-acting beta2-adrenergic agonist (LABA) medicines, such as olodaterol (one of the medicines in STIOLTO RESPIMAT), without also using a medicine called an inhaled corticosteroid, have an increased risk of serious problems from asthma, including being hospitalized, needing a tube placed in their airway to help them breathe, or death.
- call your healthcare provider if breathing problems worsen over time while using STIOLTO RESPIMAT. You may need a different treatment.
  Get emergency medical care if:
  - your breathing problems worsen quickly
  - you use your rescue inhaler medicine, but it does not relieve your breathing problems
- using too much of a LABA medicine (one of the medicines in STIOLTO RESPIMAT) may cause:

- chest pain
- fast and irregular heartbeat
- tremor

- increased blood pressure
- headache
- nervousness

- COPD symptoms can get worse over time. If your COPD symptoms worsen over time, do not increase your dose of STIOLTO RESPIMAT, instead call your healthcare provider.
- serious allergic reactions including rash, hives, itching, swelling of the face, lips, tongue, throat, difficulties in breathing or swallowing. Stop taking STIOLTO RESPIMAT and get emergency medical help right away if you get any symptoms of a serious allergic reaction after using STIOLTO RESPIMAT.
- sudden shortness of breath can happen immediately after using STIOLTO RESPIMAT. Sudden shortness of breath may be life-threatening. Stop taking STIOLTO RESPIMAT and call your healthcare provider or get emergency medical help right away if you get sudden shortness of breath after using STIOLTO RESPIMAT.
- effects on your heart, including fast or irregular heartbeat, palpitations, chest pain, and increased blood pressure.
- new or worsening eye problems including acute narrow-angle glaucoma. Symptoms of acute narrow-angle glaucoma include eye pain or discomfort, blurred vision, seeing halos or colored images around lights, and red eyes. Call your healthcare provider right away if you have any of these symptoms. Use caution as some of these eye problems can affect your ability to drive and operate appliances and machinery.
- new or worsening urinary retention. Symptoms of urinary retention may include difficulty urinating, painful urination, urinating frequently, or urinating in a weak stream or drips. Call your healthcare provider right away if you have any of these symptoms.
- changes in laboratory blood levels including high blood sugar (hyperglycemia) and low levels of potassium (hypokalemia), which may cause symptoms of muscle weakness or abnormal heart rhythm.

Common side effects of STIOLTO RESPIMAT include runny nose, cough, and back pain.
These are not all the side effects of STIOLTO RESPIMAT. Call your doctor for medical advice about side effects. You may report side effects to FDA at 1-800-FDA-1088.

How should I store STIOLTO RESPIMAT?

- Store STIOLTO RESPIMAT at room temperature, between 68°F to 77°F (20°C to 25°C).
- Do not freeze your STIOLTO cartridge or RESPIMAT inhaler.
- Keep your STIOLTO RESPIMAT inhaler, cartridge, and all medicines out of the reach of children.

General information about the safe and effective use of STIOLTO RESPIMAT
Medicines are sometimes prescribed for purposes other than those listed in a Patient Information leaflet. Do not use STIOLTO RESPIMAT for a condition for which it was not prescribed. Do not give STIOLTO RESPIMAT to other people, even if they have the same symptoms that you have. It may harm them.
You can ask your healthcare provider or pharmacist for information about STIOLTO RESPIMAT that is written for health professionals.

Active ingredients: tiotropium bromide and olodaterol
Inactive ingredients: benzalkonium chloride, edetate disodium, hydrochloric acid, and water for injection
Distributed by:
Boehringer Ingelheim Pharmaceuticals, Inc.
Ridgefield, CT 06877 USA
Licensed from:
Boehringer Ingelheim International GmbH
SPIRIVA®, HANDIHALER®, STIOLTO® and RESPIMAT® are registered trademarks of and are used under license from Boehringer Ingelheim International GmbH
Copyright © 2025 Boehringer Ingelheim International GmbH
ALL RIGHTS RESERVED
COL10537BA092025
For more information about STIOLTO RESPIMAT, including current prescribing information, a video demonstration or a Quick Start Guide on how to use STIOLTO RESPIMAT, go to www.STIOLTO.com, scan the code, or call 1-800-542-6257.

This Patient Information has been approved by the U.S. Food and Drug Administration

Revised: 1/2025

Instructions for Use
STIOLTO® RESPIMAT® (sti-OL-to- RES peh mat)
(tiotropium bromide and olodaterol inhalation spray), for oral inhalation use

For Oral Inhalation Only
Do not spray STIOLTO RESPIMAT into your eyes.
Read these Instructions for Use before you start using STIOLTO RESPIMAT and each time you get a refill. There may be new information. This leaflet does not take the place of talking to your doctor about your medical condition or your treatment.

You will need to use this inhaler 1 time each day, at the same time each day. Each time you use it take 2 puffs.

Do not turn the clear base before inserting the cartridge.

How to store your STIOLTO RESPIMAT inhaler

- Store STIOLTO RESPIMAT at room temperature between 68°F to 77°F (20°C to 25°C).
- Do not freeze your STIOLTO RESPIMAT cartridge and inhaler.
- If STIOLTO RESPIMAT has not been used for more than 3 days, release 1 puff towards the ground.
- If STIOLTO RESPIMAT has not been used for more than 21 days, repeat steps 4 to 6 under the "Prepare for first use" until a mist is visible. Then repeat steps 4 to 6 three more times.
- Keep your STIOLTO RESPIMAT cartridge, inhaler, and all medicines out of the reach of children.

How to care for your STIOLTO RESPIMAT inhaler

Clean the mouthpiece, including the metal part inside the mouthpiece, with a damp cloth or tissue only, at least 1 time each week. Any minor discoloration in the mouthpiece does not affect your STIOLTO RESPIMAT inhaler.

When to get a new STIOLTO RESPIMAT inhaler

- The scale on your inhaler will show the number of puffs you have, if used as indicated (2 puffs 1 time each day).
- The dose indicator will show you approximately how much medicine is left.
- When the dose indicator enters the red area of the scale, it will show you approximately how many puffs are left before you need a refill or new prescription.
- When the dose indicator reaches the end of the red scale, your STIOLTO RESPIMAT is empty and automatically locks. At this point, the clear base cannot be turned any further.

- Three months after insertion of cartridge, throw away the STIOLTO RESPIMAT even if it has not been used, or when the inhaler is locked, or when it expires, whichever comes first.

Prepare for first use

1. Remove clear base

- Keep the cap closed.
- Press the safety catch while firmly pulling off the clear base with your other hand. Be careful not to touch the piercing element.
- Write the discard by date on the label (3 months from the date the cartridge is inserted).

2. Insert cartridge

- Insert the narrow end of the cartridge into the inhaler.
- Place the inhaler on a firm surface and push down firmly until it clicks into place.

3. Replace clear base

- Put the clear base back into place until it clicks.
- Do not remove the clear base or the cartridge after it has been put together.

4. Turn

- Keep the cap closed.
- Turn the clear base in the direction of the arrows on the label until it clicks (half a turn).

5. Open

- Open the cap until it snaps fully open.

6. Press

- Point the inhaler toward the ground.
- Press the dose-release button.
- Close the cap.
- If you do not see a mist, repeat steps 4 to 6 until a mist is seen.
- After a mist is seen, repeat steps 4 to 6 three more times.
- After complete preparation of your inhaler, it will be ready to deliver the number of puffs on the label.

Daily use (T O P)

Turn

- Keep the cap closed.
- Turn the clear base in the direction of the arrows on the label until it clicks (half a turn).

Open

- Open the cap until it snaps fully open.

Press

- Breathe out slowly and fully.
- Close your lips around the mouthpiece without covering the air vents.
- Point the inhaler to the back of your throat.
- While taking a slow, deep breath through your mouth, Press the dose-release button and continue to breathe in.
- Hold your breath for 10 seconds or for as long as comfortable.
- Repeat Turn, Open, Press (TOP) for a total of 2 puffs.
- Close the cap until you use your inhaler again.

Answers to Common Questions

It is difficult to insert the cartridge deep enough:

Did you accidentally turn the clear base before inserting the cartridge? Open the cap, press the dose-release button, then insert the cartridge.

Did you insert the cartridge with the wide end first? Insert the cartridge with the narrow end first.

I cannot press the dose-release button:

Did you turn the clear base? If not, turn the clear base in a continuous movement until it clicks (half a turn).

Is the dose indicator on the STIOLTO RESPIMAT pointing to 0 (zero)? The STIOLTO RESPIMAT inhaler is locked after the labeled number of puffs have been used. Prepare and use your new STIOLTO RESPIMAT inhaler.

I cannot turn the clear base:

Did you turn the clear base already? If the clear base has already been turned, follow steps "Open" and "Press" under "Daily use" to get your medicine.

Is the dose indicator on the STIOLTO RESPIMAT pointing to 0 (zero)? The STIOLTO RESPIMAT inhaler is locked after the labeled number of puffs have been used. Prepare and use your new STIOLTO RESPIMAT inhaler.

The dose indicator on the STIOLTO RESPIMAT reaches 0 (zero) too soon:

Did you use STIOLTO RESPIMAT as indicated (2 puffs 1 time each day)? STIOLTO RESPIMAT will deliver the labeled number of puffs if used at 2 puffs 1 time each day.

Did you turn the clear base before you inserted the cartridge? The dose indicator counts each turn of the clear base regardless whether a cartridge has been inserted or not.

Did you spray in the air often to check whether the STIOLTO RESPIMAT is working? After you have prepared STIOLTO RESPIMAT, no test-spraying is required if used daily.

Did you insert the cartridge into a used STIOLTO RESPIMAT? Always insert a new cartridge into a NEW STIOLTO RESPIMAT.

My STIOLTO RESPIMAT sprays automatically:

Was the cap open when you turned the clear base? Close the cap, then turn the clear base.

Did you press the dose-release button when turning the clear base? Close the cap, so the dose-release button is covered, then turn the clear base.

Did you stop when turning the clear base before it clicked? Turn the clear base in a continuous movement until it clicks (half a turn).

My STIOLTO RESPIMAT does not spray:

Did you insert a cartridge? If not, insert a cartridge.

Did you repeat Turn, Open, Press (TOP) less than 3 times after inserting the cartridge? Repeat Turn, Open, Press (TOP) 3 times after inserting the cartridge as shown in steps 4 to 6 under "Prepare for first use".

Is the dose indicator on the STIOLTO RESPIMAT pointing to 0 (zero)? You have used up all your medicine and the inhaler is locked.

For more information about STIOLTO RESPIMAT, including current prescribing information, a video demonstration or a Quick Start Guide on how to use STIOLTO RESPIMAT, go to www.STIOLTO.com, scan the code, or call 1-800-542-6257.

This Patient Information and Instructions for Use has been approved by the U.S. Food and Drug Administration.

Distributed by: Boehringer Ingelheim Pharmaceuticals, Inc., Ridgefield, CT 06877 USA

Licensed from:
Boehringer Ingelheim International GmbH

SPIRIVA®, HANDIHALER®, STIOLTO® and RESPIMAT® are registered trademarks of and are used under license from Boehringer Ingelheim International GmbH

Copyright © 2025 Boehringer Ingelheim International GmbH
ALL RIGHTS RESERVED

Revised: January 2025

COL10537BA092025

PRINCIPAL DISPLAY PANEL - 2.5 mcg/2.5 mcg Cartridge Carton

NDC 0597-0155-61

Stiolto® Respimat®
(tiotropium bromide and olodaterol
inhalation spray)

2.5 mcg/2.5 mcg per actuation*

FOR ORAL INHALATION ONLY

ATTENTION PHARMACIST:
Dispense with Instructions for Use

Rx only

4 Grams
60 Metered Inhalations
(Two inhalations equal one dose)

Boehringer
Ingelheim